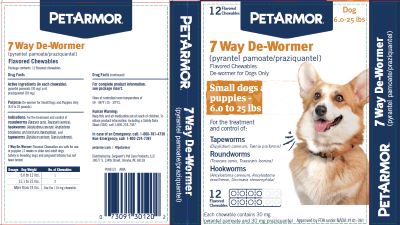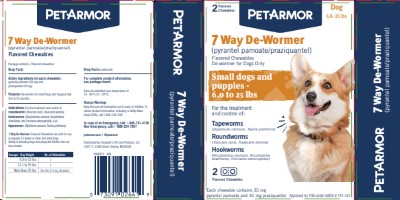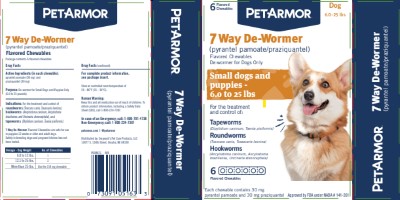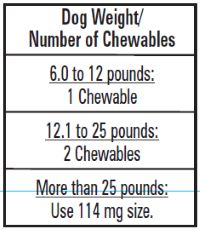 DRUG LABEL: 7 Way De-Wormer
NDC: 21091-641 | Form: TABLET, CHEWABLE
Manufacturer: Sergeant's Pet Care Products Inc.
Category: animal | Type: OTC ANIMAL DRUG LABEL
Date: 20260121

ACTIVE INGREDIENTS: PYRANTEL PAMOATE 30 mg/1 1; PRAZIQUANTEL 30 mg/1 1

7 Way De-Wormer (pyrantel pamoate/praziquantel) Flavored Chewables

Package contents:

blisters of 2, 6 or 12 flavored chewables

Drug Facts

Active Ingredients (in each chewable): Pyrantel Pamoate (30 mg) and Praziquantel (30 mg)

Purpose: Dewormer for Puppies and Small Dogs Only (6.0 to 25 pounds)

Uses: For the treatment and control of

• Tapeworms (Dipylidium caninum, Taenia pisiformis)
• Roundworms (Toxocara canis, Toxascaris leonina)
• Hookworms (Ancylostoma caninum, Ancylostoma braziliense, and Uncinaria stenocephala)

Human Warning:

Keep this and all medication out of the reach of children. To obtain product information, including a Safety Data Sheet (SDS), call 1-800-224-7387.

When Using This Product:

• Consult your veterinarian for assistance in the diagnosis, treatment, and control of parasitism.

• Do not de-worm a dog or puppy that is sick. Consult a veterinarian for diagnosis of the illness.

• 7 Way De-Wormer Flavored Chewables are safe for use in puppies 12 weeks or older and adult dogs. Safety in breeding dogs and pregnant bitches has not been tested.

You May Notice:

Vomiting, loose stools (with or without blood) and decreased activity following treatment. If you notice these signs, contact a veterinarian.

Directions:

Each flavored chewable contains 30 mg of pyrantel pamoate and 30 mg of praziquantel. The dose for each drug is 2.27 mg per pound of body weight (5 mg/kg). Please refer to the following dosing table for help finding the right dose for your dog.

7 Way De-Wormer Flavored Chewables Dosing Table

• You should weigh your dog to make sure you are giving the right dose.

• 7 Way De-Wormer Flavored Chewables are palatable if offered by hand. If your dog does not voluntarily eat the chewable, you can hide the chewable in a small amount of food or place it in the back of the dog's mouth for forced swallowing.

• Make sure that the dog eats the complete dose.

• Watch your dog for a few minutes after dosing to make sure the chewable is not rejected.

Other Information:

Recommended Deworming Schedule: Consult your veterinarian for assistance in the diagnosis, treatment, and control of parasitism. Deworming schedules may vary depending on the climate where you live and the activity of your dog.

Re-treatment: Re-treatment of your dog may be necessary as determined by laboratory fecal examination and/or if your dog is living where re-infections are likely to occur. Consult your veterinarian for assistance in the diagnosis and prevention of re-infection. In case of re-infection with tapeworms (Dipylidium caninum), consult your veterinarian for advice on how to remove fleas from the dog and the environment.

Storage:

Store at controlled room temperature of 15-30oC (59-86oF).

Questions? Comments?

To report suspected adverse drug events or for technical assistance, contact Virbac AH, Inc. at 1-800-338-3659 or us.virbac.com. For additional information about adverse drug experience reporting for animal drugs, contact FDA at 1-888-FDA-VETS or www.fda.gov/reportanimalae.

Distributed by

Sergeant's Pet Care Products, LLC
10077 South 134th Street
Omaha, NE 68138
Approved by FDA under NADA # 141-261

P008078 AMIA